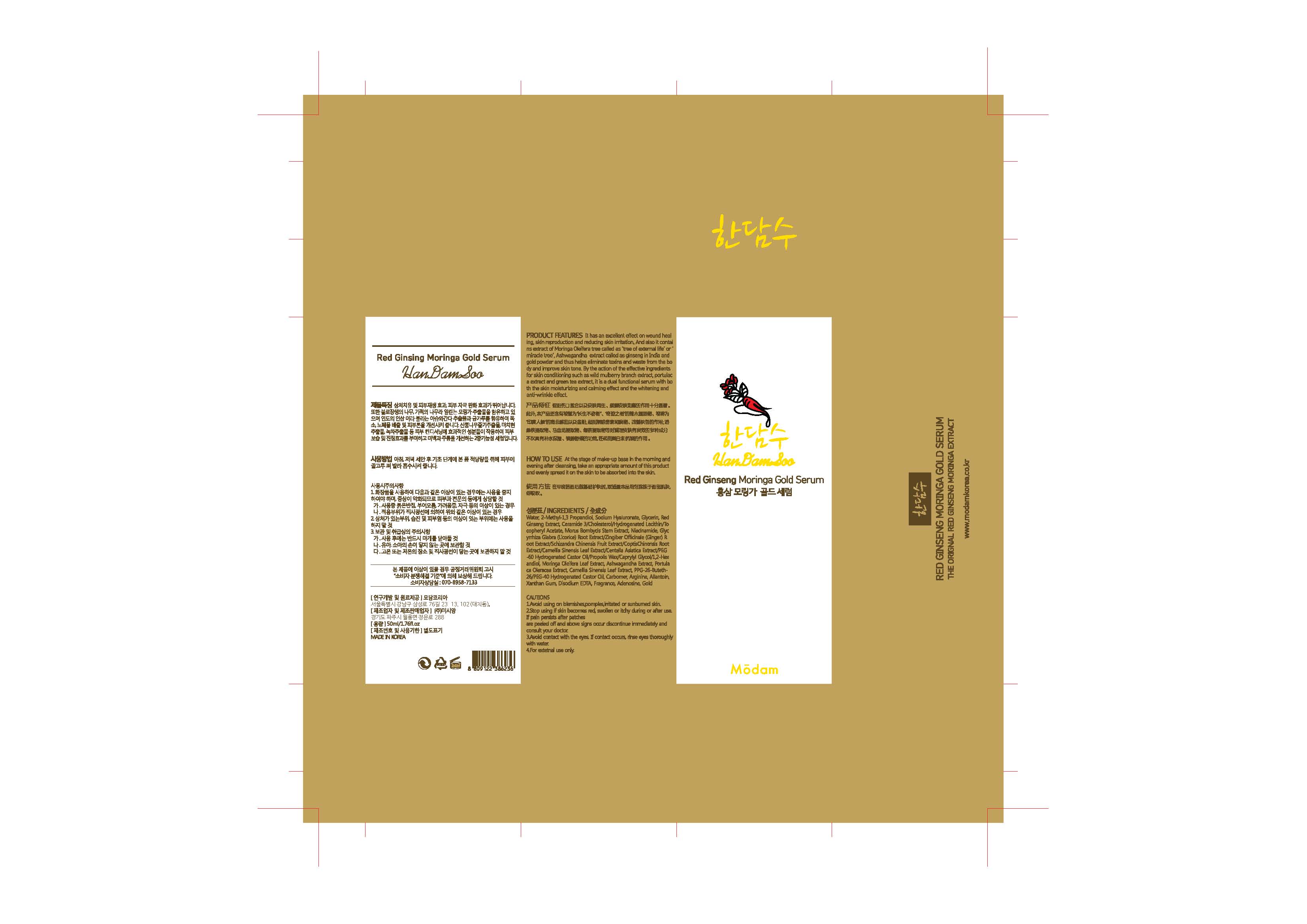 DRUG LABEL: Red Ginseng Snail Gold Serum
NDC: 72540-002 | Form: LIQUID
Manufacturer: MODAM KOREA
Category: otc | Type: HUMAN OTC DRUG LABEL
Date: 20190508

ACTIVE INGREDIENTS: GLYCERIN 12.75 g/150 mL; Allantoin 0.15 g/150 mL
INACTIVE INGREDIENTS: Water; Methylpropanediol; Butylene Glycol; Niacinamide; Cholesterol; Propylene Glycol; PPG-26-Buteth-26; Arginine; 1,2-Hexanediol; Xanthan Gum; Propolis Wax; Caprylyl Glycol; Adenosine; Phenoxyethanol; Gold

ACTIVE INGREDIENT

Glycerin (8.5%) - Skin Protectact

Allantoin (0.1%) - Skin Protectact

INACTIVE INGREDIENT

Water, Methylpropanediol, Red Ginseng Extract, Ceramide Ⅲ, Butylene Glycol, Niacinamide, Cholesterol, Morus Bombycis Stem Extract, Propylene Glycol, Withania Somnifera Root Extract, Snail Secretion Filtrate, PPG-26-Buteth-26, Carbomer, Arginine, Camellia Sinensis Leaf Extract, Moringa Pterygosperma Seed Extract, Portulaca Oleracea Extract, PEG-40 Hydrogenated Castor Oil, Hydrogenated Lecithin, 1,2-Hexanediol, Centella Asiatica Extract, Coptis Chinensis Root Extract, Glycyrrhiza Glabra (Licorice) Root Extract, Schizandra Chinensis Fruit Extract, Xanthan Gum
Zingiber Officinale (Ginger) Root Extract, PEG-60 Hydrogenated Castor Oil, Ethyl Hexanediol, Propolis Wax, Caprylyl Glycol, Disodium EDTA, Fragrance, Adenosine, Tocopheryl Acetate, Phenoxyethanol, Gold

PURPOSE

Skin Protectact

WARNINGS

Cautions
1. Avoid using on blemishes, pimples, irritated or sunburned skin.
2. Stop using if skin becomes red, swollen or itchy during or after use. If pain persists after patches are peeled off and above signs occur discontinue immediately and consult your doctor.
3. Avoid contact with the eyes. If contact occurs, rinse eyes thoroughly with water.
4. For external use only.

INDICATIONS & USAGE

At the stage of make-up base in the morning and evening after cleansing, take an appropriate amount of this product and evenly spread it on the skin to be absorbed into the skin.

DOSAGE & ADMINISTRATION

At the stage of make-up base in the morning and evening after cleansing, take an appropriate amount of this product and evenly spread it on the skin to be absorbed into the skin.